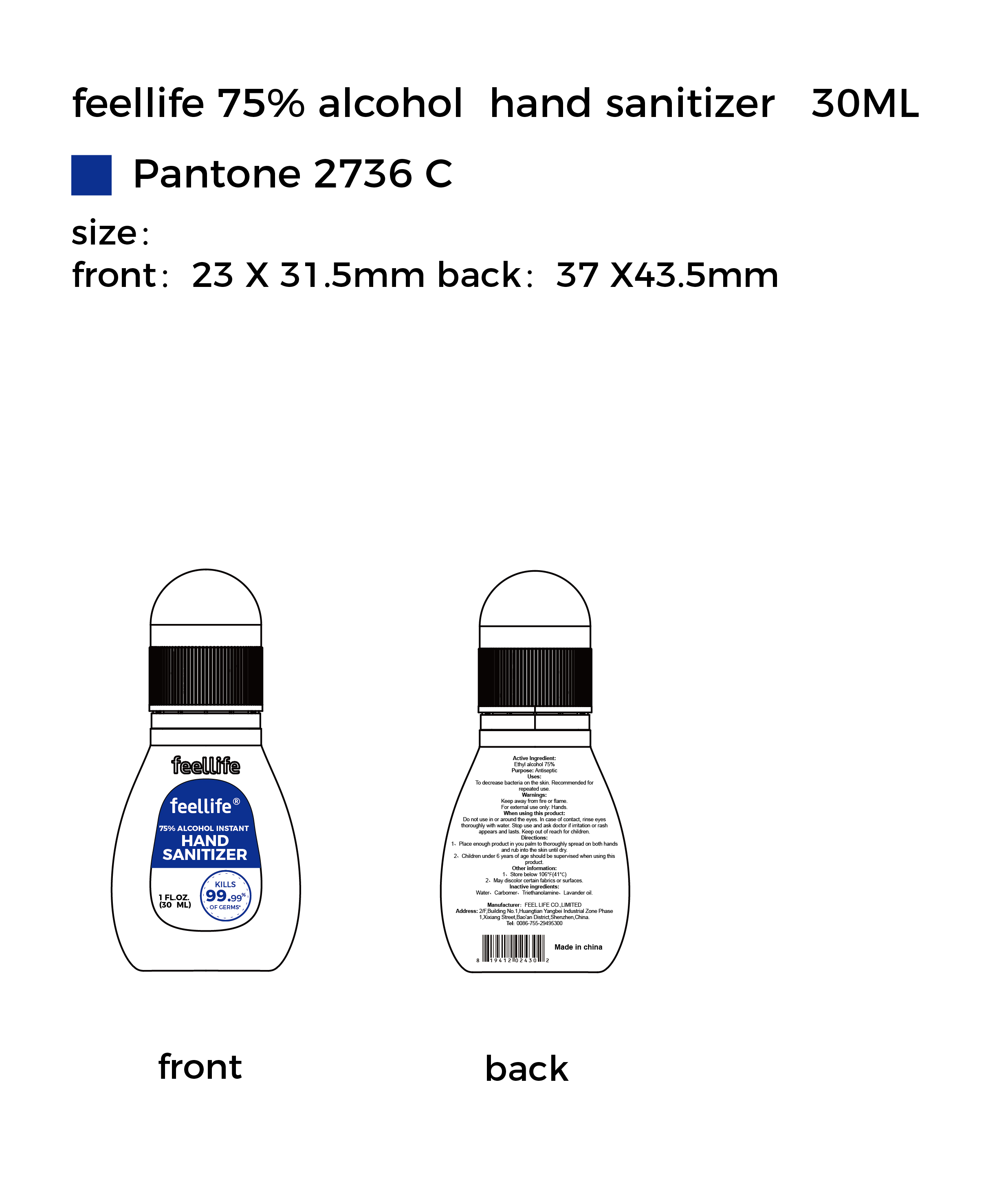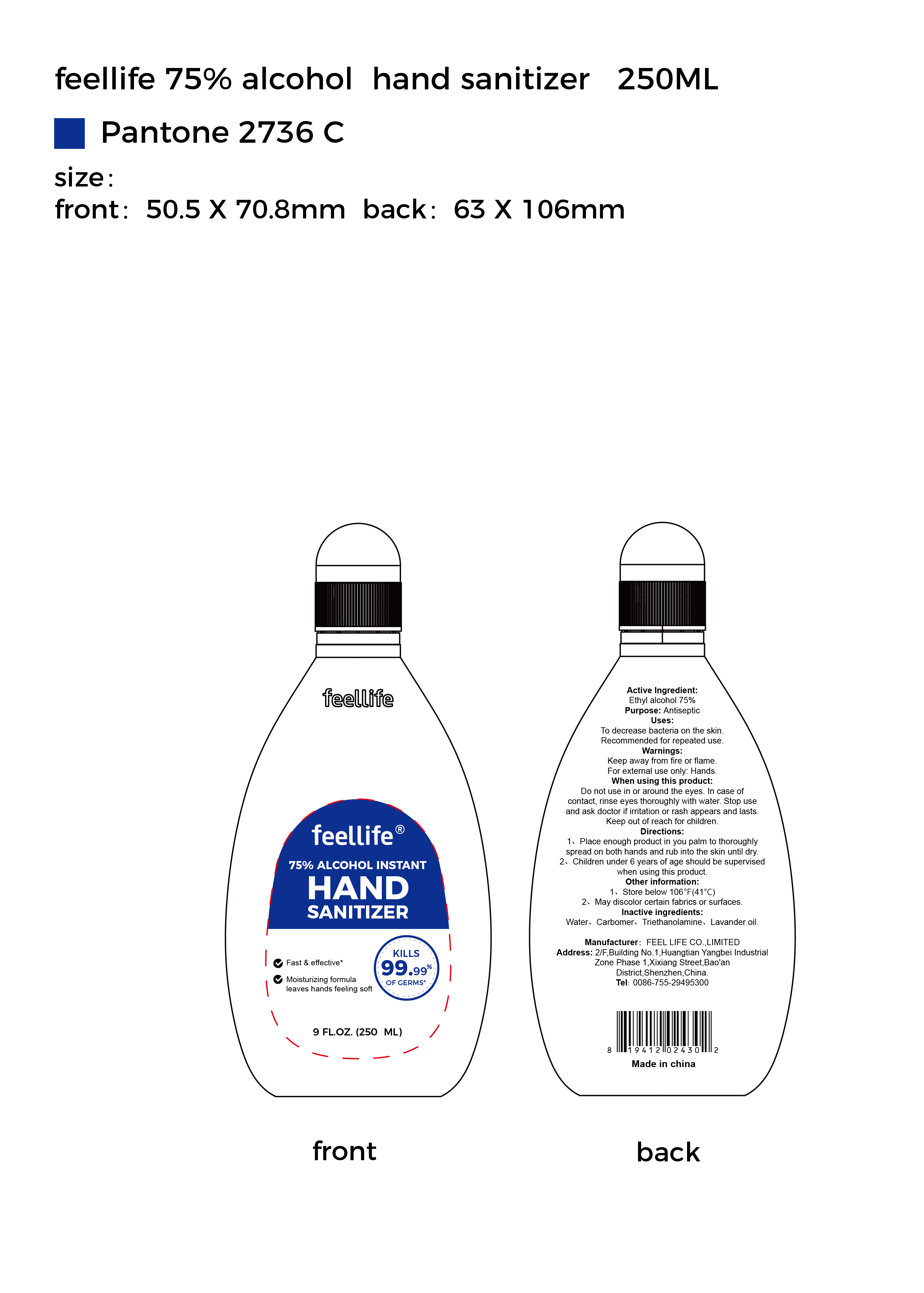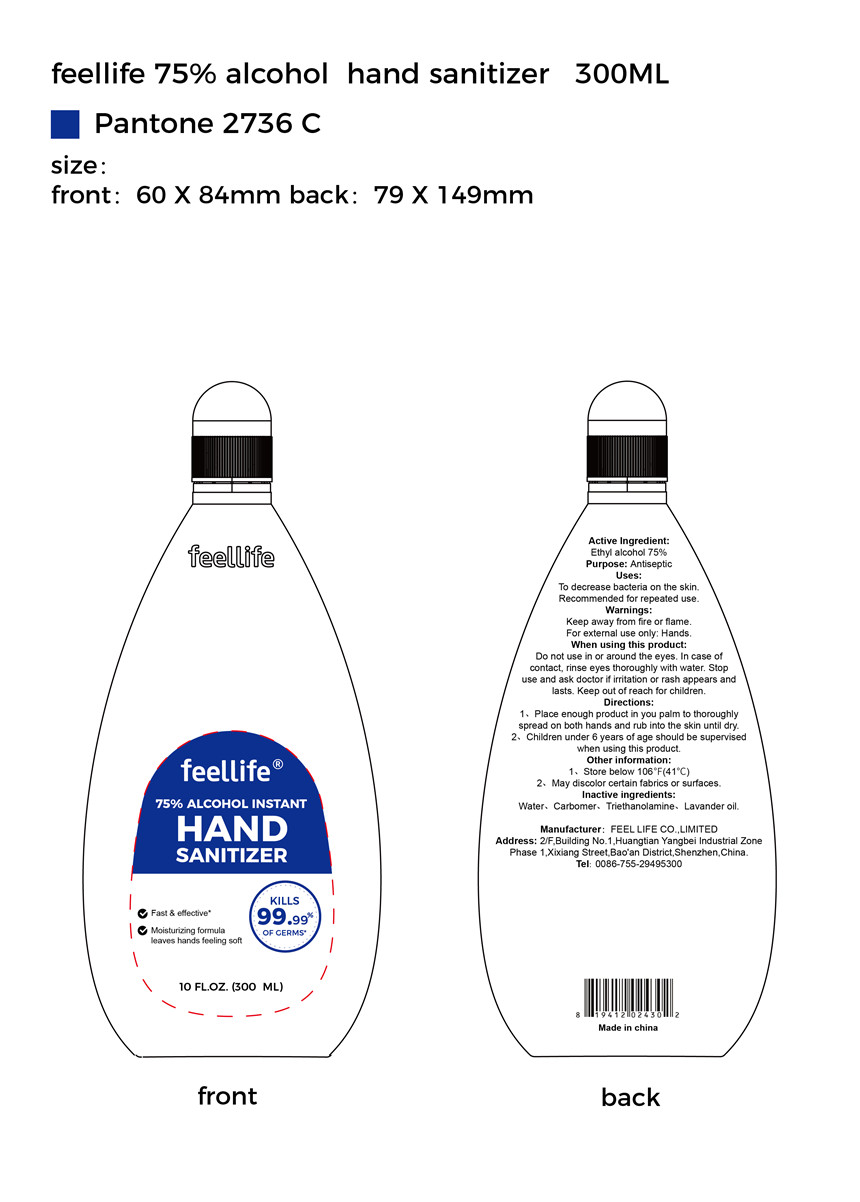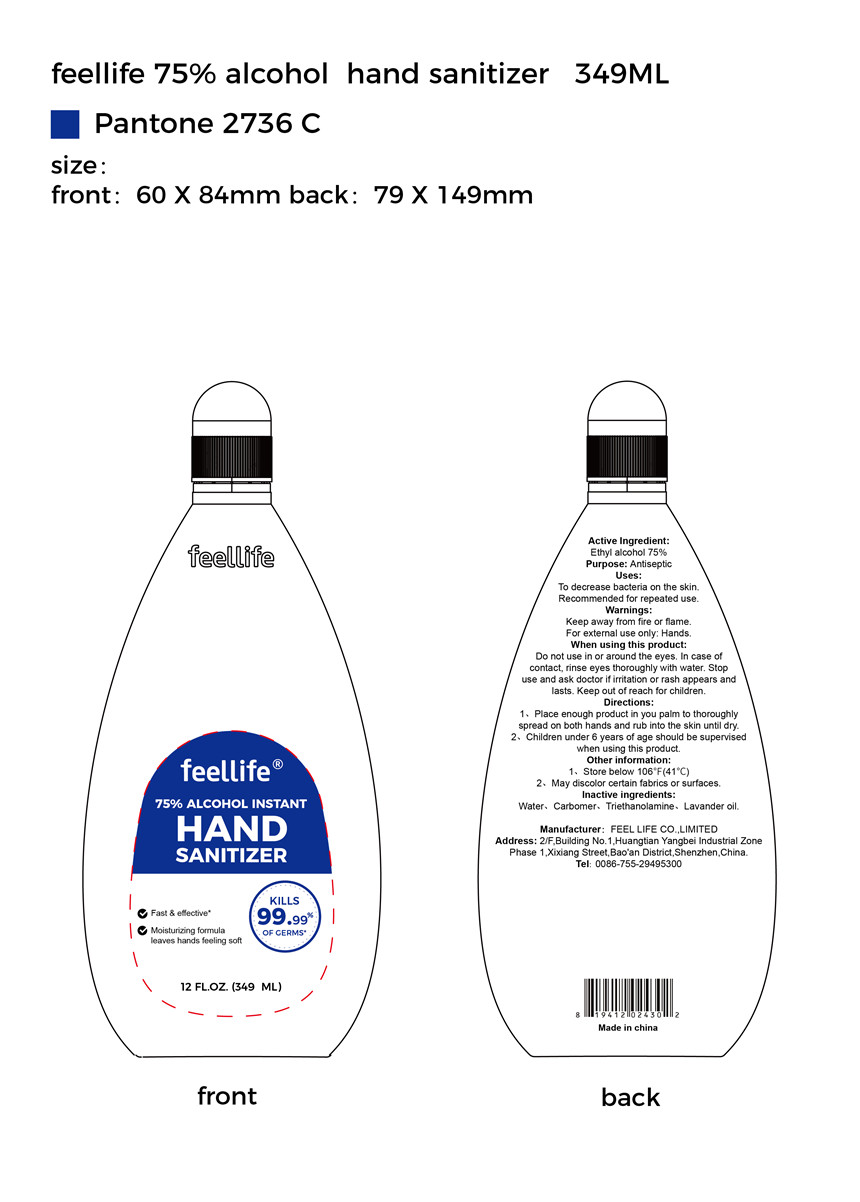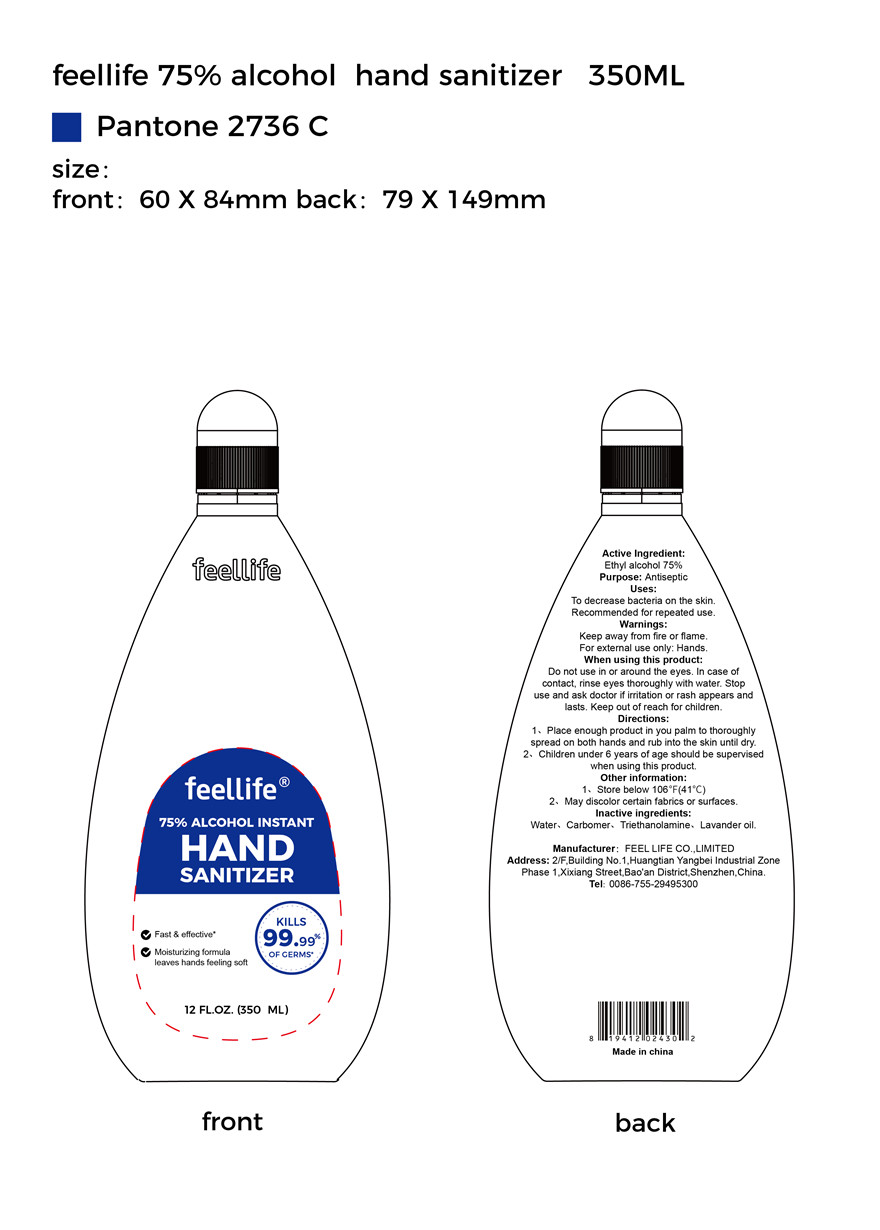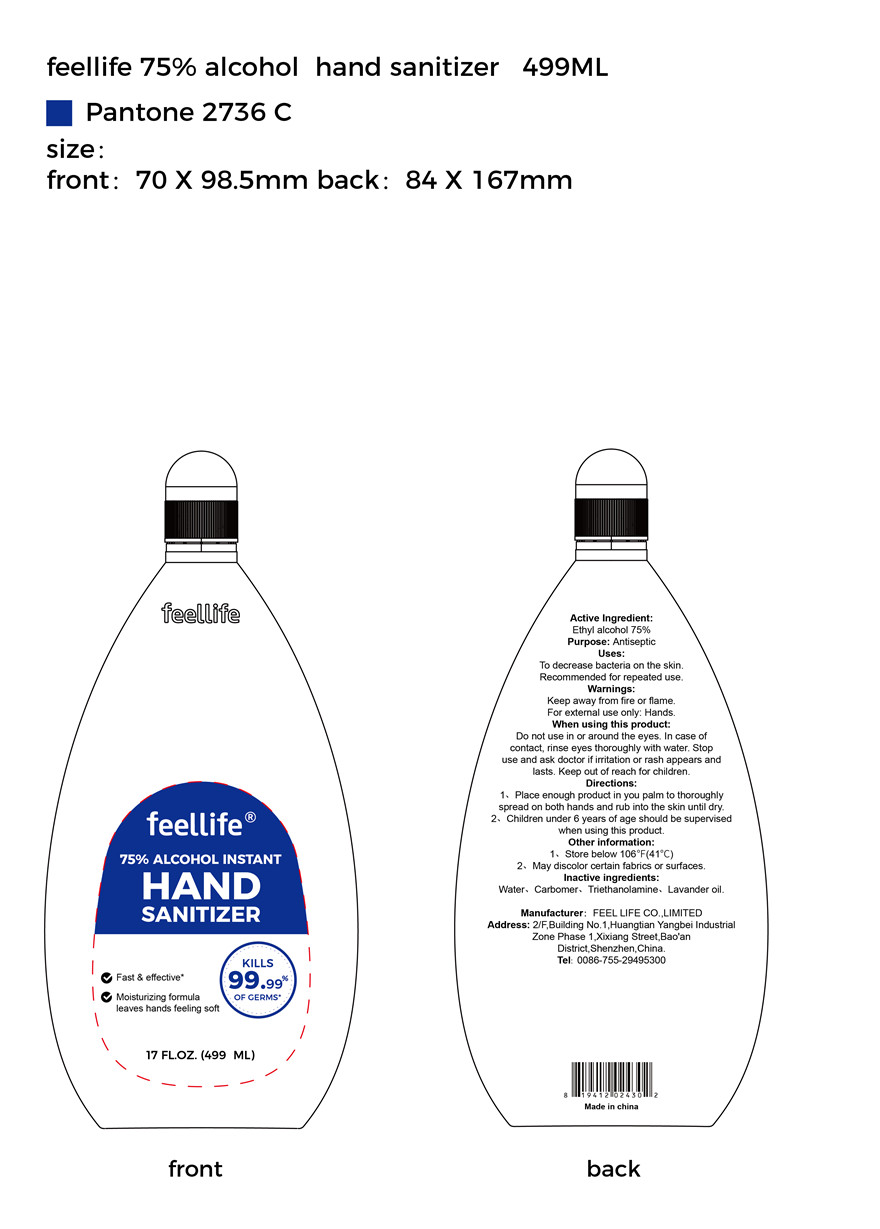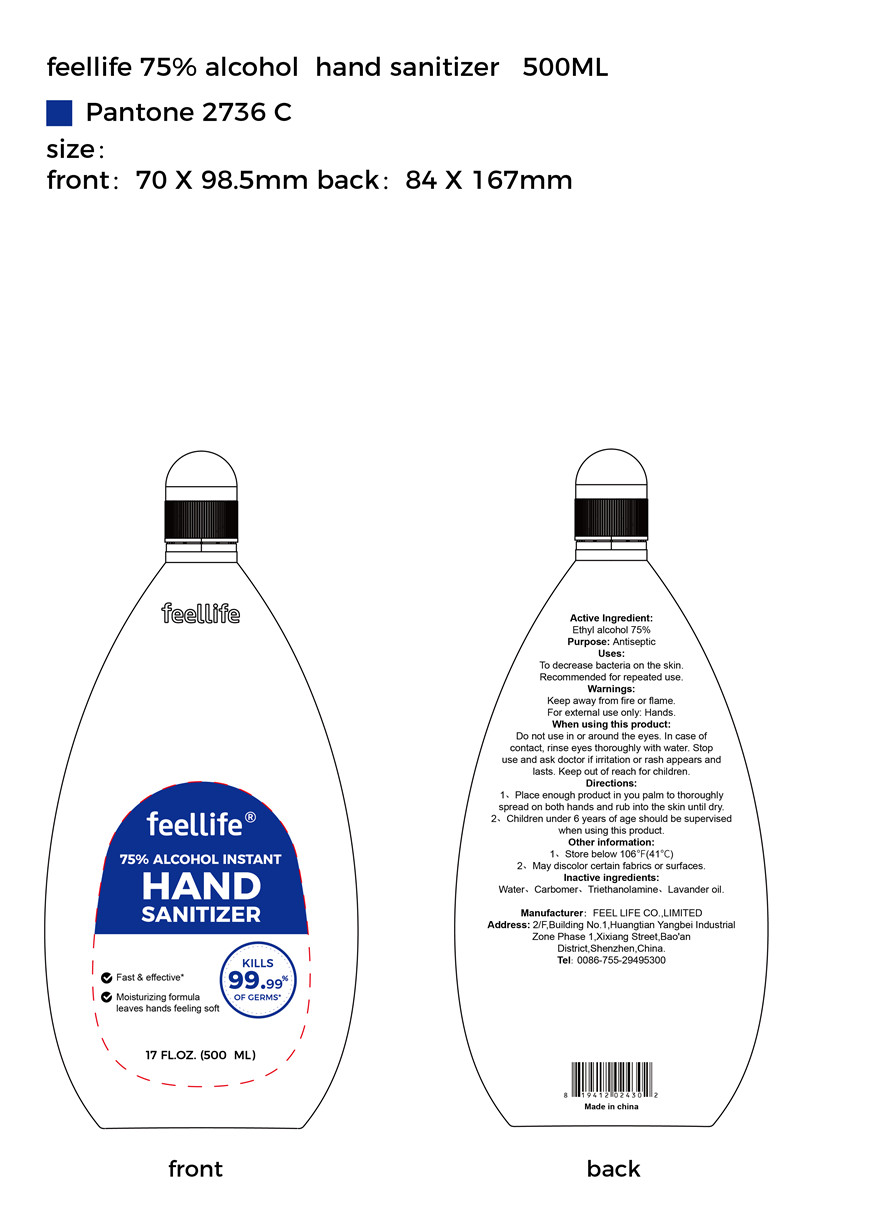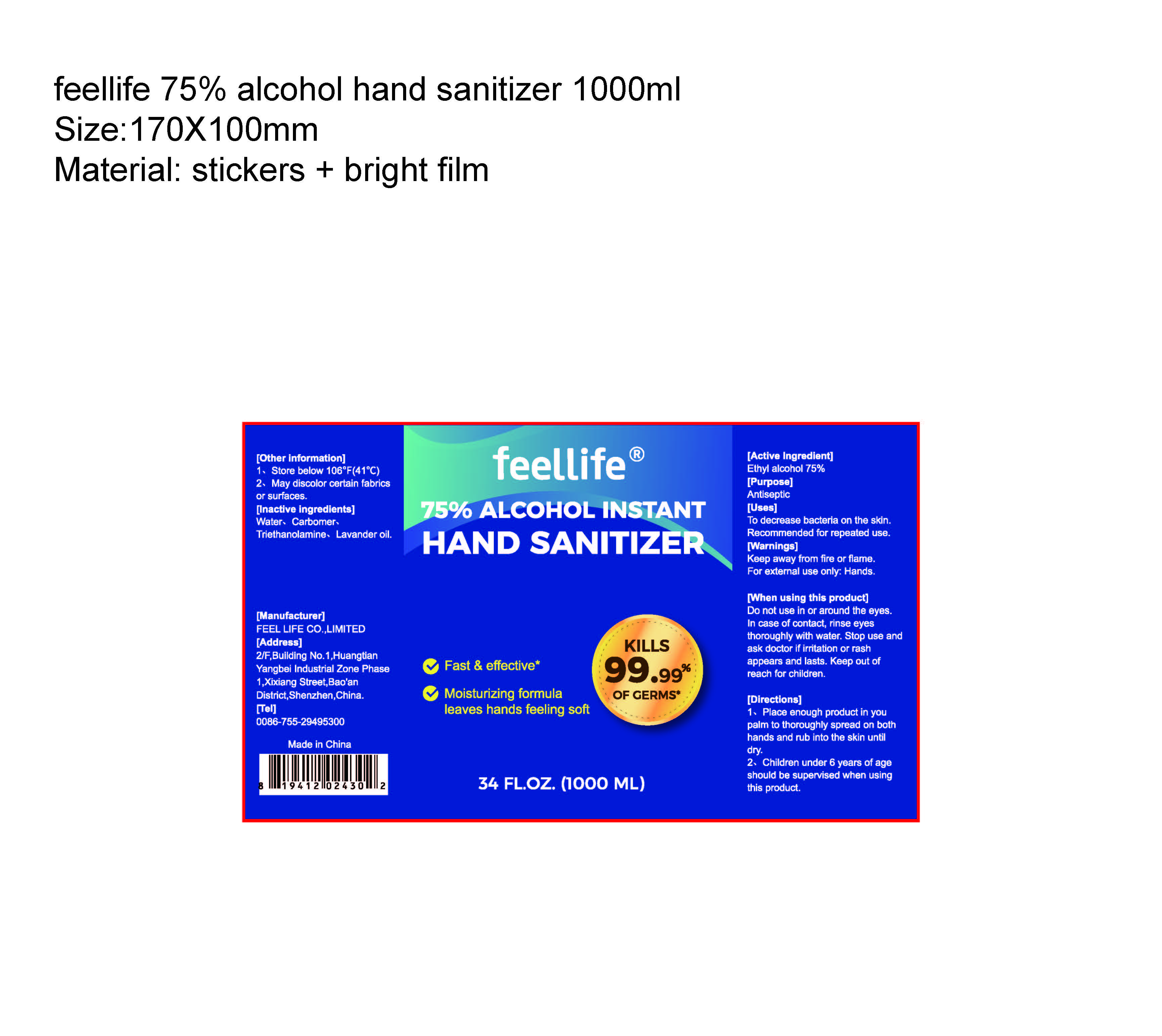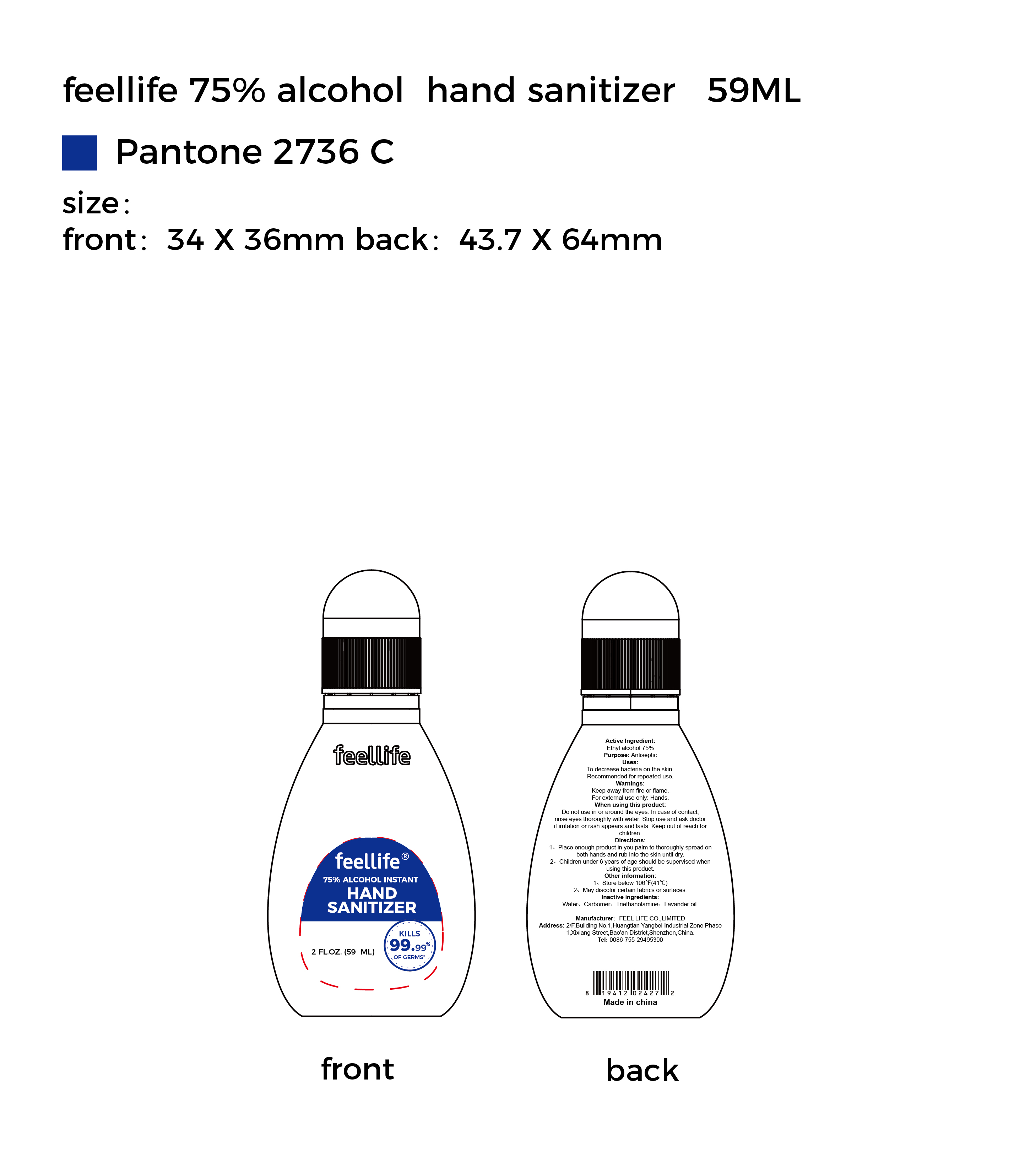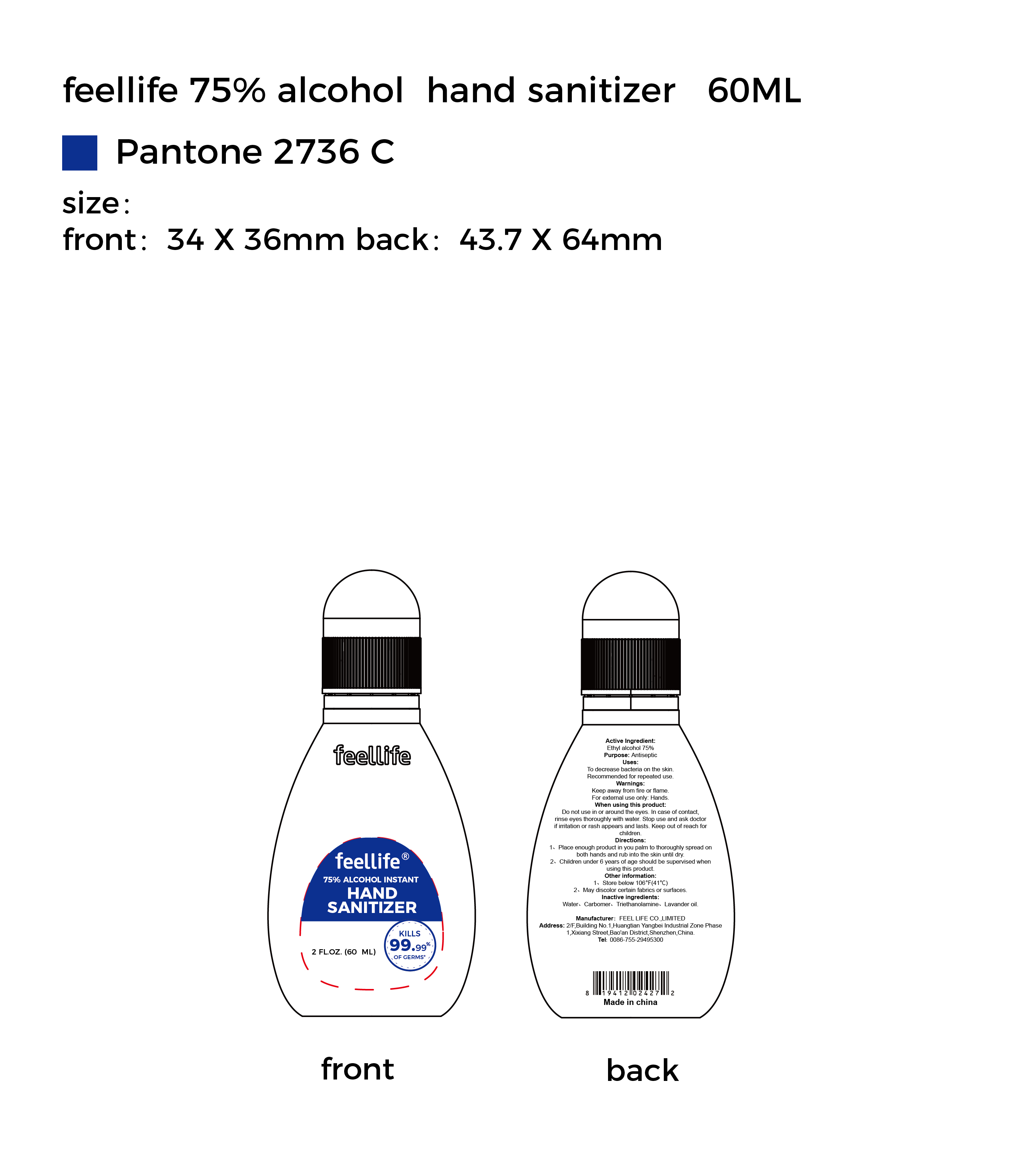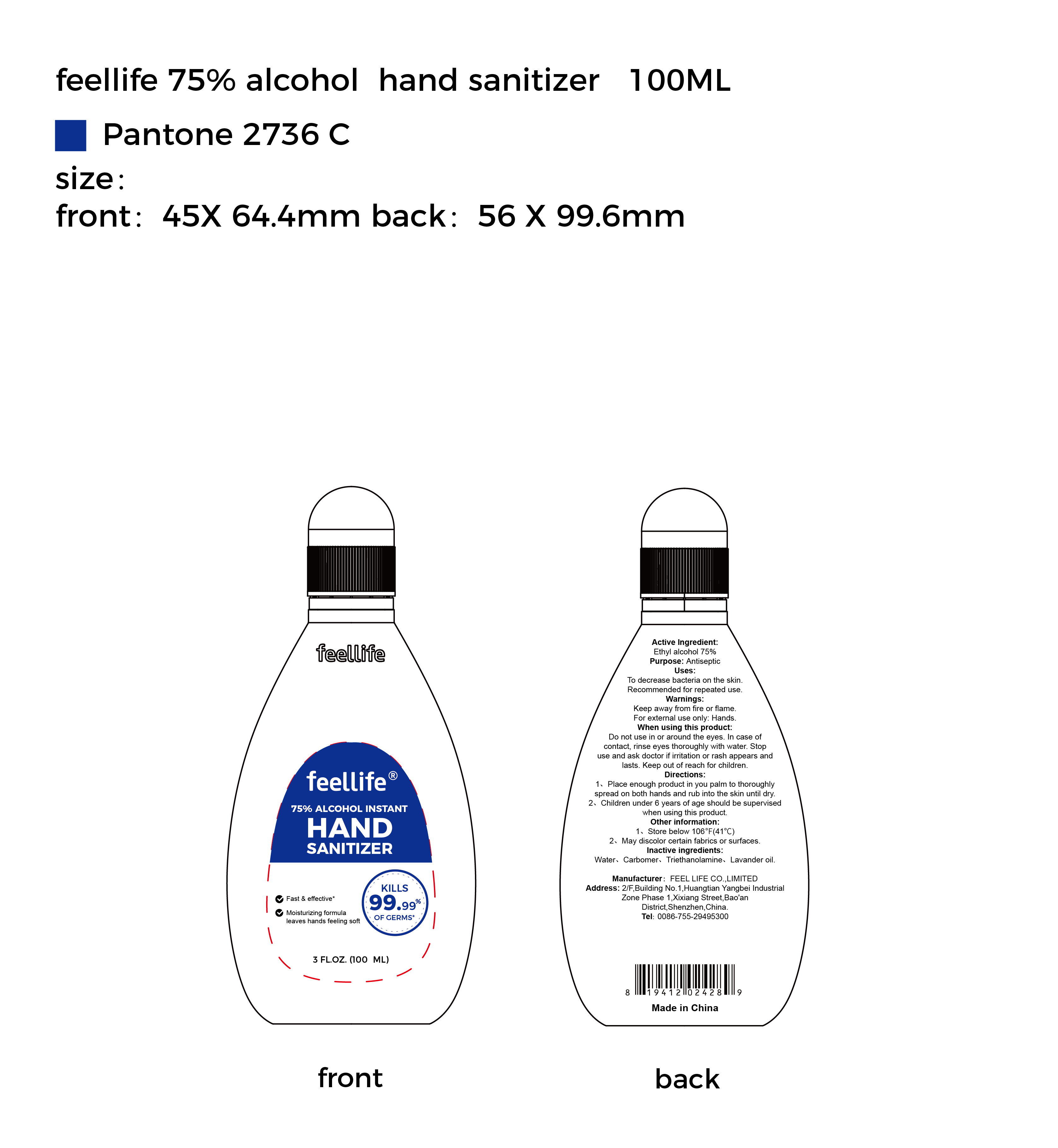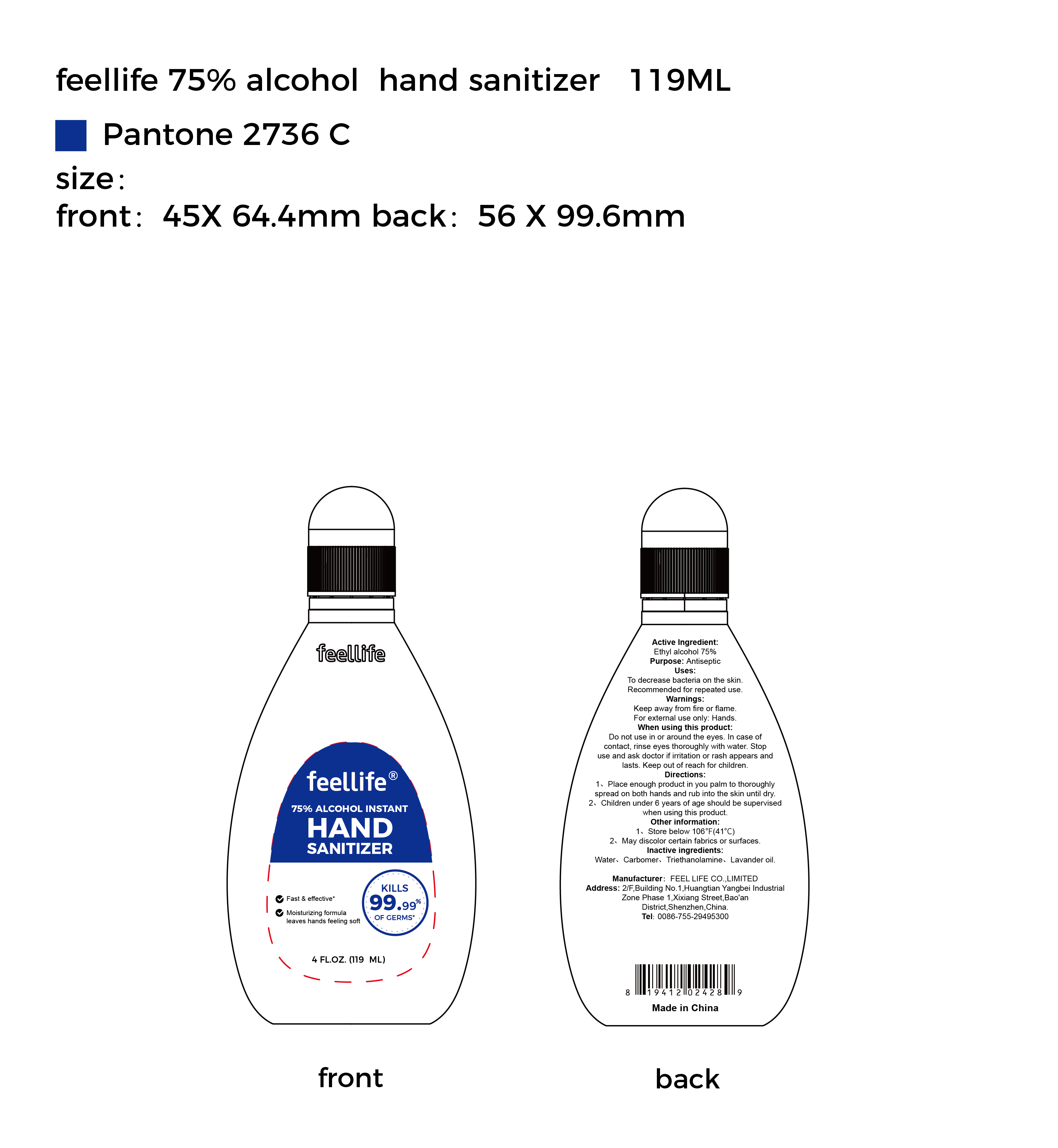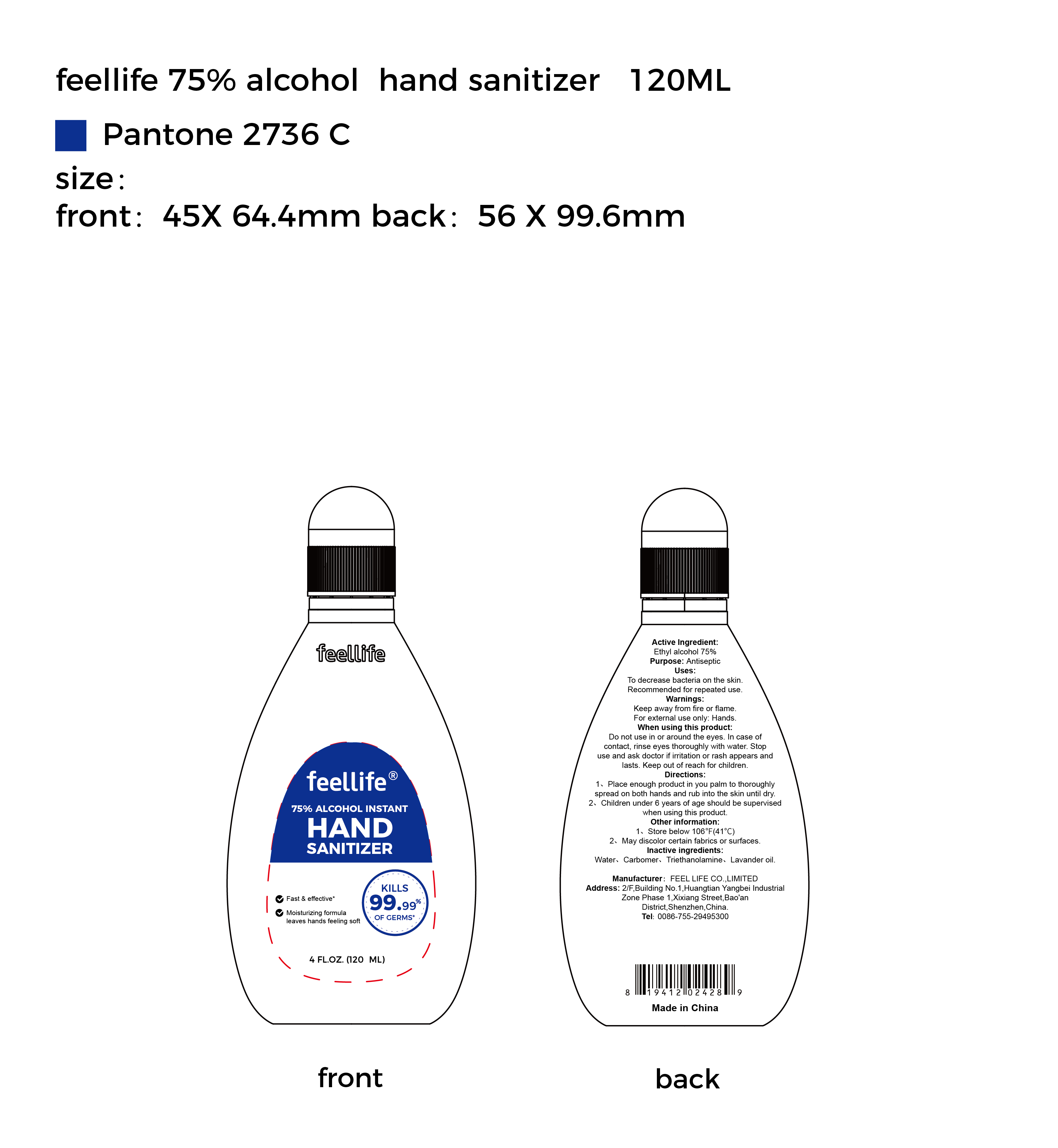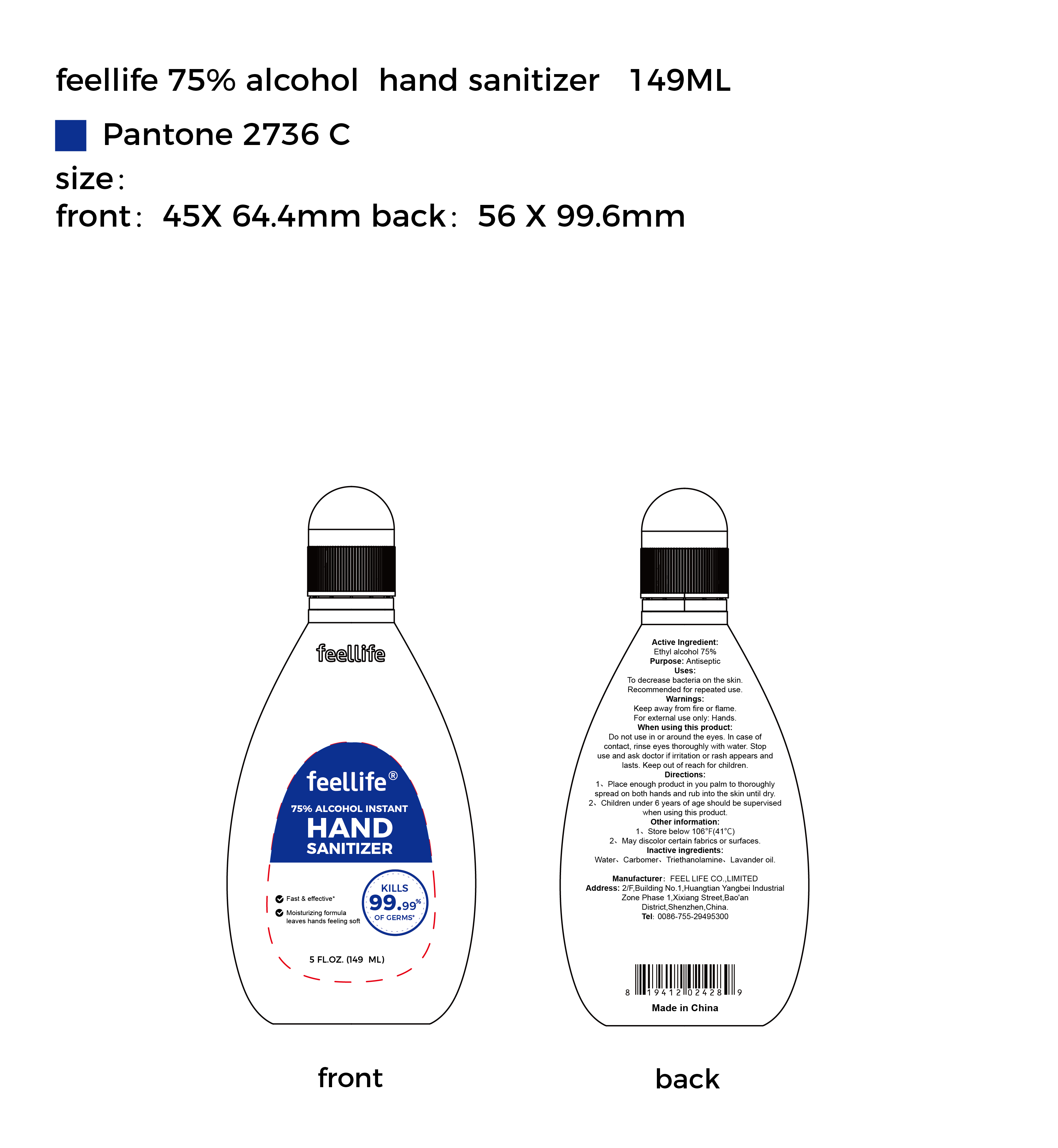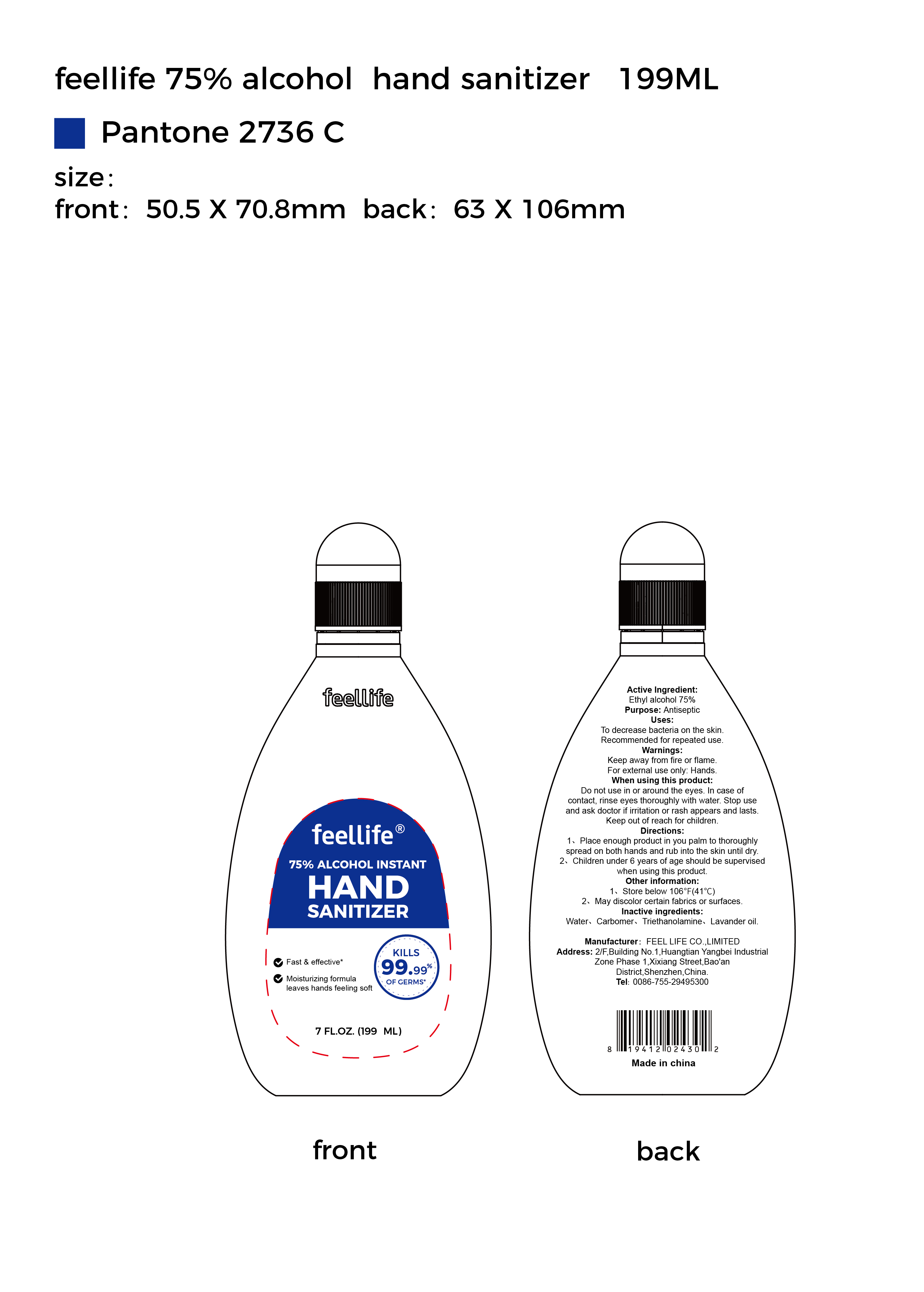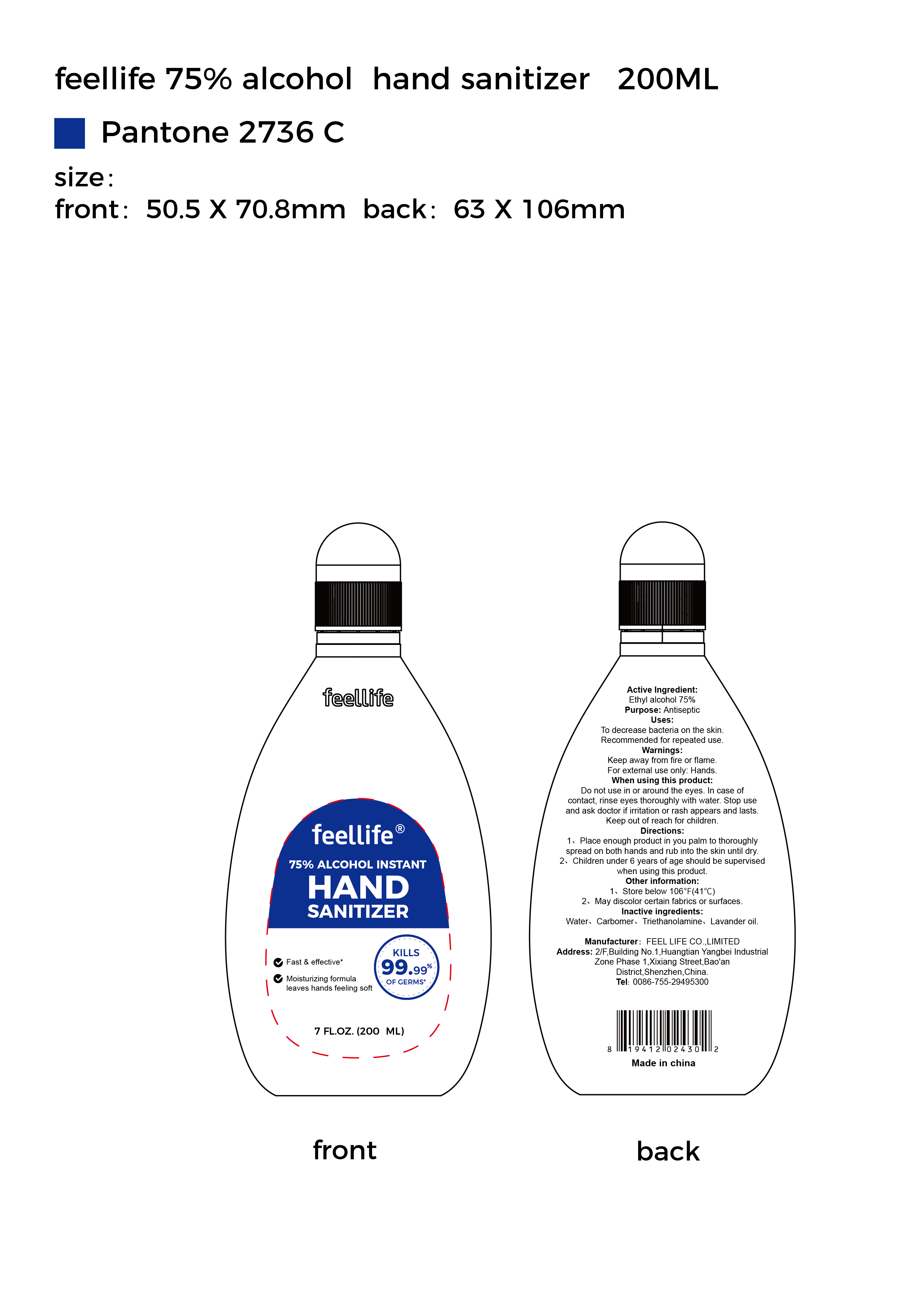 DRUG LABEL: 75% Alcohol Instant Hand Sanitizer
NDC: 75879-001 | Form: GEL
Manufacturer: FEEL LIFE CO.,LIMITED
Category: otc | Type: HUMAN OTC DRUG LABEL
Date: 20200511

ACTIVE INGREDIENTS: ALCOHOL 75 mL/100 mL
INACTIVE INGREDIENTS: CARBOMER HOMOPOLYMER, UNSPECIFIED TYPE; TROLAMINE; WATER

75% Alcohol Instant Hand Sanitizer

Active Ingredient

Ethyl alcohol 75%

Purpose

Antiseptic

Uses

To decrease bacteria on the skin.Recommended for repeated use.

Warnings

Keep away from fire or flame.

For external use only:Hands

When using this product

Do not use in or around the eyes.In case of contact, rinse eyes thoroughly with water.Stop use and ask doctor if irritation or rash

appears and lasts.Keep out of reach for children.

Directions

1.Place enough product in you palm to thoroughly spread on both hands

and rub into the skin until dry.

2.Children under 6 years of age should be supervised when using this product.

Other information

1.Store below 106°F(41℃)

2.May discolor certain fabrics or surfaces

Inactive ingredients

Water、Carbomer、Triethanolamine、Lavander oil.